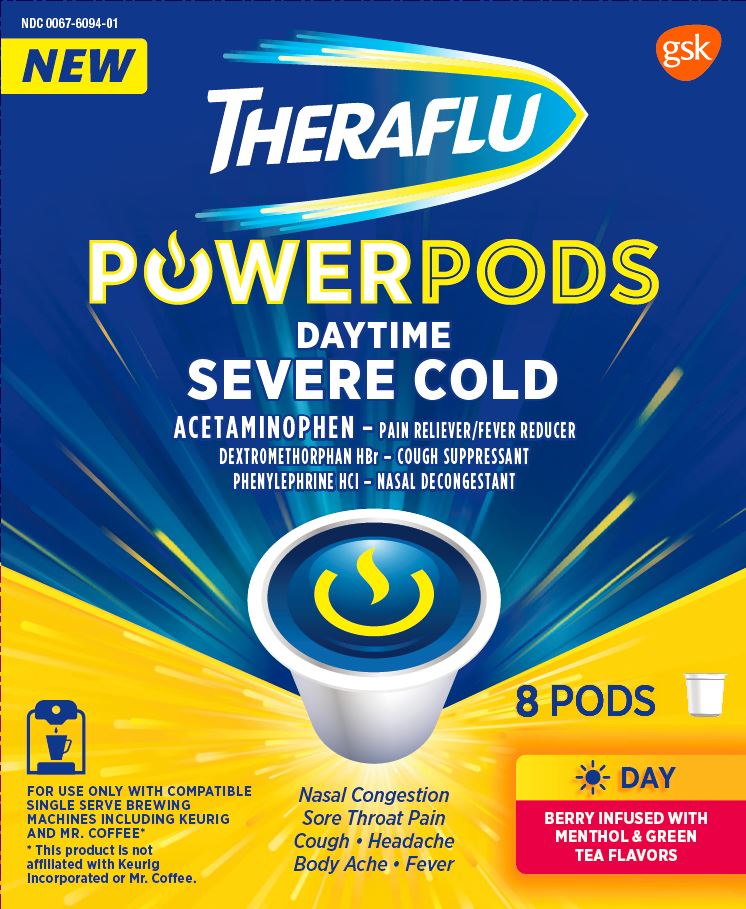 DRUG LABEL: Theraflu

NDC: 0067-6094 | Form: POWDER, FOR SOLUTION
Manufacturer: Haleon US Holdings LLC
Category: otc | Type: HUMAN OTC DRUG LABEL
Date: 20240308

ACTIVE INGREDIENTS: ACETAMINOPHEN 650 mg/1 1; DEXTROMETHORPHAN HYDROBROMIDE 20 mg/1 1; PHENYLEPHRINE HYDROCHLORIDE 10 mg/1 1
INACTIVE INGREDIENTS: ACESULFAME POTASSIUM; ANHYDROUS CITRIC ACID; ASPARTAME; FD&C BLUE NO. 1; FD&C RED NO. 40; MALTODEXTRIN; SILICON DIOXIDE; SODIUM CITRATE, UNSPECIFIED FORM; SUCROSE; TRIBASIC CALCIUM PHOSPHATE

Drug Facts

Active ingredients (in each pod)

Acetaminophen 650 mg

Dextromethorphan HBr 20 mg

Phenylephrine HCl 10 mg

Purposes

Pain reliever/Fever reducer

Cough suppressant

Nasal decongestant

Uses

- temporarily relieves these symptoms due to a cold:
  - minor aches and pains
  - minor sore throat pain
  - headache
  - nasal and sinus congestion
  - cough due to minor throat and bronchial irritation
- temporarily reduces fever

Warnings

Liver warning:This product contains acetaminophen. Severe liver damage may occur if you take

- more than 4,000 mg of acetaminophen in 24 hours
- with other drugs containing acetaminophen
- 3 or more alcoholic drinks every day while using this product

Allergy alert:Acetaminophen may cause severe skin reactions. Symptoms may include:

- skin reddening
- blisters
- rash

If a skin reaction occurs, stop use and seek medical help right away.

Sore throat warning:If sore throat is severe, persists for more than 2 days, is accompanied or followed by fever, headache, rash, nausea, or vomiting consult a doctor promptly.

Do not use

- in a child under 12 years of age
- if you are allergic to acetaminophen
- with any other drug containing acetaminophen (prescription or nonprescription). If you are not sure whether a drug contains acetaminophen, ask a doctor or pharmacist.
- if you are now taking a prescription monoamine oxidase inhibitor (MAOI) (certain drugs for depression, psychiatric, or emotional conditions, or Parkinson's disease), or for 2 weeks after stopping the MAOI drug. If you do not know if your prescription drug contains an MAOI, ask a doctor or pharmacist before taking this product.

Ask doctor before use if you have

- liver disease
- heart disease
- high blood pressure
- thyroid disease
- diabetes
- trouble urinating due to an enlarged prostate gland
- cough that occurs with too much phlegm (mucus)
- cough that lasts or is chronic such as occurs with smoking, asthma or emphysema

Ask a doctor or pharmacist before use if you are

- taking the blood thinning drug warfarin

When using this product

- do not exceed recommended dosage

Stop use and ask a doctor if

- nervousness, dizziness, or sleeplessness occurs
- fever gets worse or lasts more than 3 days
- redness or swelling is present
- new symptoms occur
- pain, cough or nasal congestion gets worse or lasts more than 7 days
- cough comes back or occurs with rash or headache that lasts. These could be signs of a serious condition.

If pregnant or breast-feeding,

ask a health professional before use.

Keep out of reach of children.

In case of overdose, get medical help or contact a Poison Control Center right away. Prompt medical attention is critical for adults as well as for children even if you do not notice any signs or symptoms.

Directions

- do not use more than directed
- take every 4 hours, while symptoms persist. Do not take more than 5 pods in 24 hours unless directed by a doctor.

Age | Dose
adults and children 12 years of age and over | one pod
children under 12 years of age | do not use

- do not remove the foil seal as the pod will not work properly and could result in hot water burns
- place pod in compatible brewer
- use a minimum of 8 oz. of water
- when finished, the pod will be hot and may drip. Tilt the pod during removal to avoid dripping.
- remove used pod and flush brewer after use with a minimum of 8 oz. of water
- sip while hot. Consume entire drink within 10-15 minutes.

Other information

- each pod contains:potassium 10 mg, sodium 20 mg
- phenylketonurics:contains phenylalanine 14 mg per pod
- do not open pouch until time of use
- store at controlled room temperature 20o-25oC (68o-77oF). Protect product from heat and moisture.

Inactive ingredients

acesulfame potassium, anhydrous citric acid, aspartame, FD&C blue no. 1, FD&C red no. 40, flavors, maltodextrin, silicon dioxide, sodium citrate, sucrose, tribasic calcium phosphate

Questions or comments?

call 1-855-328-5259

Principal Display

NDC 0067-6094-01

NEW

THERAFLU

POWERPODS

DAYTIME

SEVERE COLD

ACETAMINOPHEN – PAIN RELIEVER/FEVER REDUCER

DEXTROMETHORPHAN HBr – COUGH SUPPRESSANT

PHENYLEPHRINE HCl – NASAL DECONGESTANT

- Nasal Congestion
- Sore Throat Pain
- Cough
- Headache
- Body Ache
- Fever

BERRY INFUSED WITH MENTHOL & GREEN TEA FLAVORS

8 PODS

FOR USE ONLY WITH COMPATIBLE SINGLE SERVE BREWING MACHINES INCLUDING KEURIG AND MR. COFFEE*

*This product is not affiliated with Keurig Incorporated or Mr. Coffee.

READ ALL WARNINGS AND DIRECTIONS ON CARTON BEFORE USE.

KEEP CARTON FOR REFERENCE. DO NOT DISCARD.

TAMPER EVIDENT POUCH. PRODUCT IS PACKAGED IN INDIVIDUAL SEALED POUCHES. DO NOT USE IF POUCH IS TORN OR BROKEN. DO NOT OPEN POUCH UNTIL TIME OF USE.

PARENTS:

Learn about teen medicine abuse

www.StopMedicineAbuse.org

PRESS

Press the 8 oz. setting on your machine to brew.

SIP

Sip while hot. Consume entire drink within 10-15 minutes. Remove used pod and flush brewer after use

with a minimum of 8 oz. of water.

CAUTION: PRODUCT LIQUID AND POD WILL BE HOT.

RELIEF

Prepare to experience powerful cold & flu multi-symptom relief.

1-855-328-5259

Distributed by:

GSK Consumer Healthcare,Warren, NJ 07059

©2018 GSK group of companies or its licensor.

Trademarks are owned by or licensed to the GSK group of companies.

13019